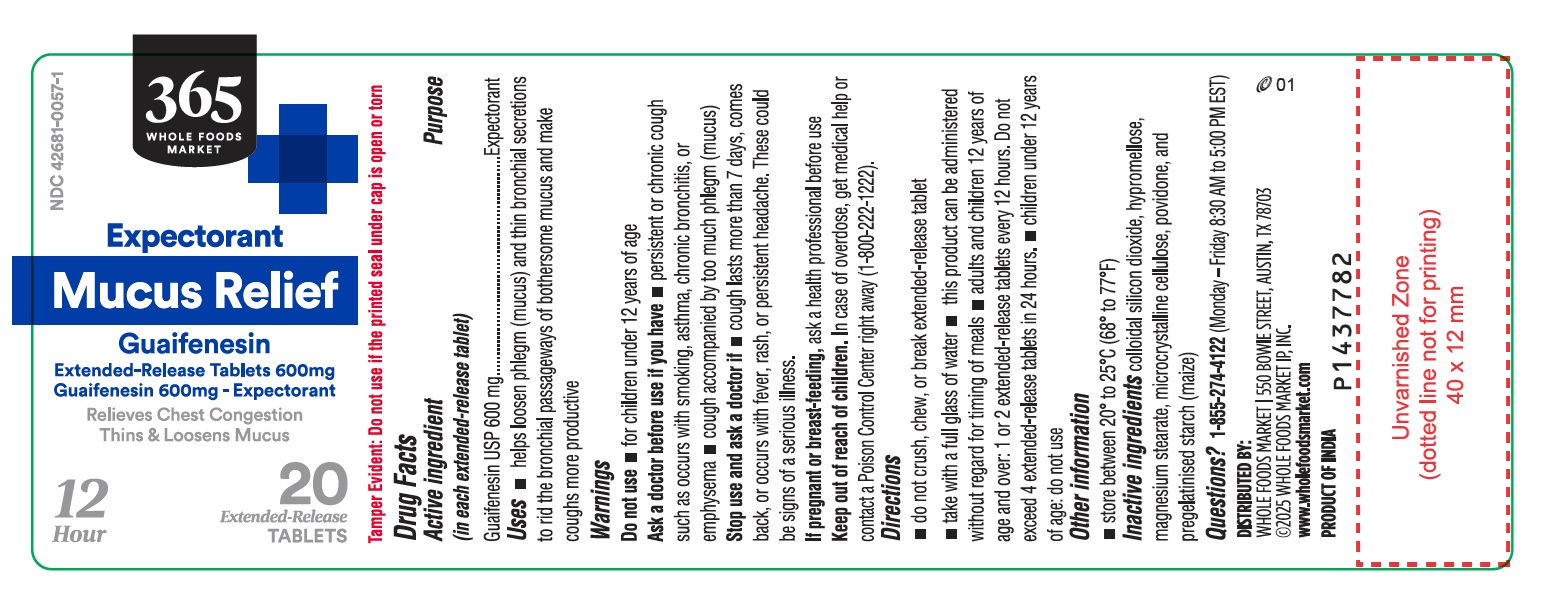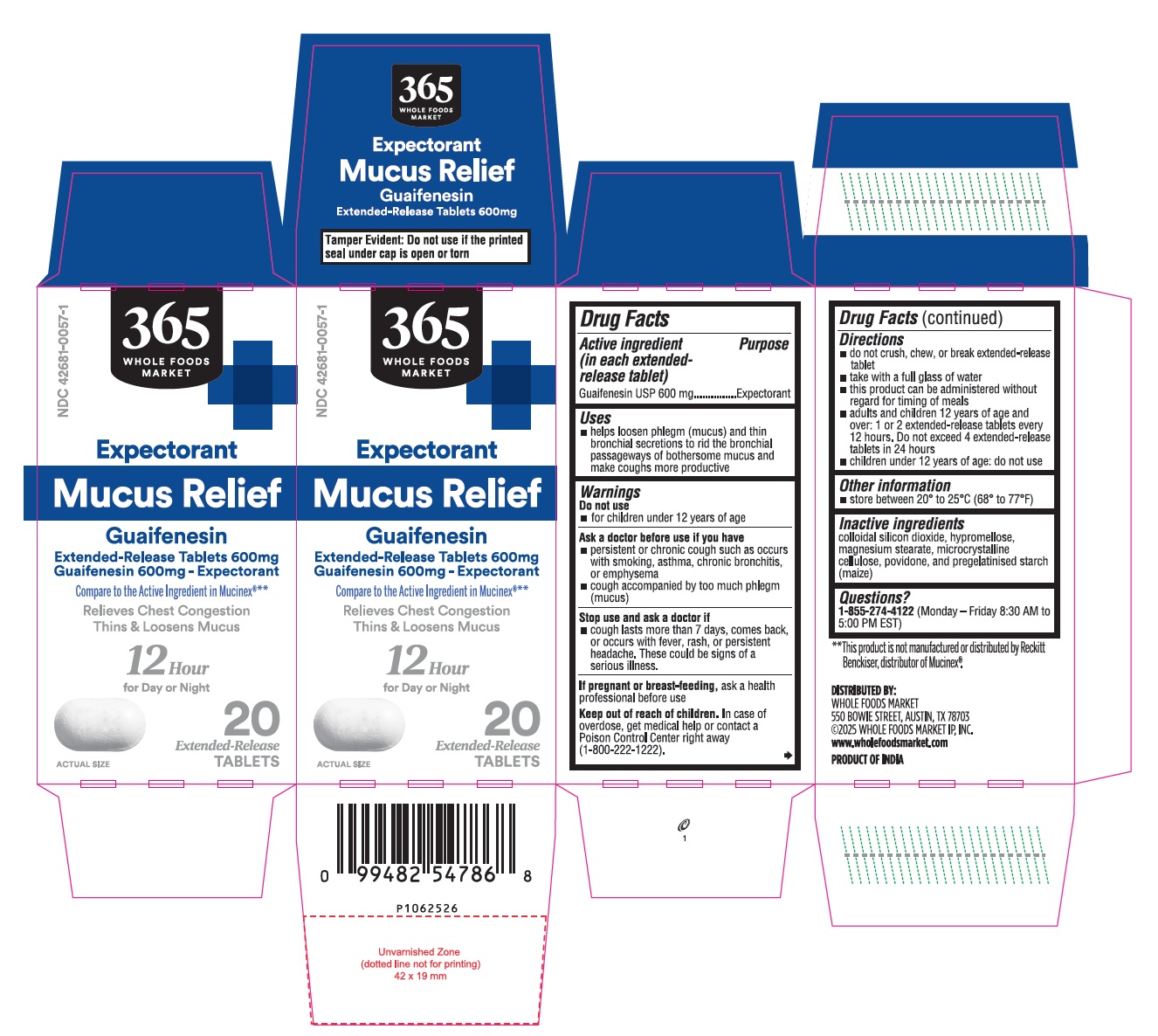 DRUG LABEL: 365 WHOLE FOODS MARKET GUAIFENESIN
NDC: 42681-0057 | Form: TABLET, EXTENDED RELEASE
Manufacturer: Whole Foods Market, Inc.
Category: otc | Type: Human OTC Drug Label
Date: 20260120

ACTIVE INGREDIENTS: GUAIFENESIN 600 mg/1 1
INACTIVE INGREDIENTS: SILICON DIOXIDE; HYPROMELLOSE 2208 (15000 MPA.S); HYPROMELLOSE 2910 (10000 MPA.S); MAGNESIUM STEARATE; MICROCRYSTALLINE CELLULOSE 101; MICROCRYSTALLINE CELLULOSE 102; POVIDONE K90; POVIDONE K25; STARCH, CORN

Drug Facts

Active ingredient

(in each extended-release tablet)
Guaifenesin USP 600 mg

Purpose

Expectorant

Uses

- helps loosen phlegm (mucus) and thin bronchial secretions to rid the bronchial passageways of bothersome mucus and make coughs more productive

Warnings

Do not use

- for children under 12 years of age

Ask a doctor before use if you have

- persistent or chronic cough such as occurs with smoking, asthma, chronic bronchitis, or emphysema
- cough accompanied by too much phlegm (mucus)

Stop use and ask a doctor if

- cough lasts more than 7 days, comes back, or occurs with fever, rash, or persistent headache. These could be signs of a serious illness.

If pregnant or breast-feeding,

ask a health professional before use

Keep out of reach of children.

In case of overdose, get medical help or contact a Poison Control Center right away (1-800-222-1222).

Directions

- do not crush, chew, or break extended-release tablet
- take with a full glass of water
- this product can be administered without regard for the timing of meals
- adults and children 12 years of age and over: 1 or 2 extended-release tablets every 12 hours. Do not exceed 4 extended-release tablets in 24 hours
- children under 12 years of age: do not use

Other information

- store between 20° to 25°C (68° to 77°F)

Inactive ingredients

colloidal silicon dioxide, hypromellose, magnesium stearate, microcrystalline cellulose, povidone, and pregelatinised starch (maize)

Questions?

1-855-274-4122 (Monday – Friday 8:30 AM to 5:00 PM EST)

DISTRIBUTED BY:
WHOLE FOODS MARKET
550 BOWIE STREET, AUSTIN, TX 78703
©2025 WHOLE FOODS MARKET IP, INC.
www.wholefoodsmarket.com
PRODUCT OF INDIA

PACKAGE LABEL-PRINCIPAL DISPLAY PANEL - 600 mg (20 Tablets Container Label)

365
WHOLE FOODS
MARKET
NDC 42681-0057-1
Expectorant
Mucus Relief
Guaifenesin
Extended-Release Tablets 600mg
Guaifenesin 600mg- Expectorant
Relieves Chest Congestion
Thins & Loosens Mucus
12 20
Hour Extended-Release
TABLETS

PACKAGE LABEL-PRINCIPAL DISPLAY PANEL - 600 mg (20 Tablets Container Carton)

365
WHOLE FOODS
MARKET
NDC 42681-0057-1
Expectorant
Mucus Relief
Guaifenesin
Extended-Release Tablets 600mg
Guaifenesin 600mg - Expectorant

Compare to the Active Ingredient in Mucinex®**

Relieves Chest Congestion
Thins & Loosens Mucus
12 Hour

for Day or Night

ACTUAL SIZE 20

Extended-Release
TABLETS